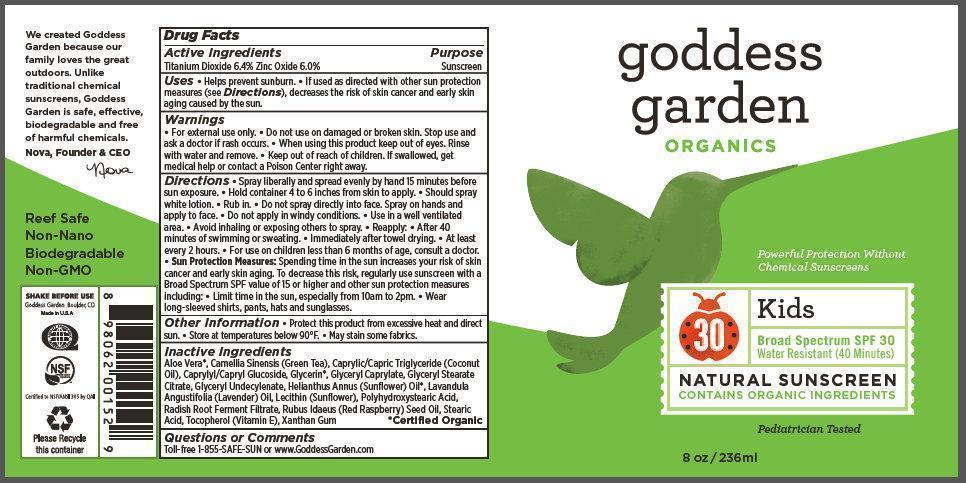 DRUG LABEL: Goddess Garden Organics Kids Natural Sunscreen
NDC: 58479-043 | Form: SPRAY
Manufacturer: Crossing Cultures, LLC dba Goddess Garden
Category: otc | Type: HUMAN OTC DRUG LABEL
Date: 20161212

ACTIVE INGREDIENTS: TITANIUM DIOXIDE 6.4 g/100 g; ZINC OXIDE 6 g/100 g
INACTIVE INGREDIENTS: SAFFLOWER OIL; LAVANDIN OIL; WATER; ALOE VERA LEAF; ALUMINUM HYDROXIDE; MEDIUM-CHAIN TRIGLYCERIDES; CAPRYLHYDROXAMIC ACID; GLYCERIN; GLYCERYL CAPRYLATE; POLYGLYCERYL-10 DECAOLEATE; GLYCERYL STEARATE CITRATE; POLYHYDROXYSTEARIC ACID (2300 MW); LAVENDER OIL; STEARIC ACID; TOCOPHEROL; XANTHAN GUM

Kids Natural Mineral Sunscreen Broad Spectrum SPF 30 Spray

Active Ingredients

Titanium Dioxide 6.4% Zinc Oxide 6.0%

Purpose

Sunscreen

Uses

• Helps prevent sunburn.

• If used as directed with other sun protection measures (see Directions), decreases the risk of skin cancer and early skin
aging caused by the sun.

Warnings

• For external use only.

Do not use

on damaged or broken skin.

Stop use and ask a doctor

if rash occurs

When using this product

keep out of eyes. Rinse with water and remove.

Keep out of reach of children.

If swallowed, get medical help or contact a Poison Center right away.

Directions

Hold container 4 to 6 inches from skin to apply. • Spray liberally and spread evenly by hand 15 minutes before sun exposure. • Should spray white lotion. • Rub in. • Shake well. Should spray white lotion. Rub in. • Do not spray directly into face. Spray on hands and apply to face. • Do not apply in windy conditions. • Use in a well ventilated area. • Avoid inhaling or exposing others to spray. • Reapply: • After 40 minutes of swimming or sweating. • Immediately after towel drying. • At least every 2 hours. • Sun Protection Measures: Spending time in the sun increases your risk of skin cancer and early skin aging. To decrease this risk, regularly use sunscreen with a Broad Spectrum SPF value of 15 or higher and other sun protection measures including: • Limit time in the sun, especially from 10am to 2pm. • Wear long-sleeved shirts, pants, hats and sunglasses. • For use on children less than 6 months of age, consult a doctor.

Other Information

• Protect this product from excessive heat and direct sun. • Store at temperatures below 90°F. • May stain some fabrics or surfaces.

Inactive Ingredients

Aloe Barbadensis Leaf Juice*, Aluminum Hydroxide, Caprylhydroxamic Acid, Caprylic/Capric Triglyceride (Coconut Oil), Carthamus Tinctorius (Safflower) Seed Oil*, Glycerin, Glyceryl Caprylate, Glyceryl Stearate Citrate, Helianthus Annuus (Sunflower) Seed Oil*, Lavandula Angustifolia (Lavender) Oil*, Lavandula Hybrida (Lavandin) Oil*, Polyglyceryl-10 Decaoleate, Polyhydroxystearic Acid, Stearic Acid, Tocopherol (Vitamin E), Water, Xanthan Gum *Certified Organic

Questions or Comments

Toll-free 1-855-SAFE-SUN or www.GoddessGarden.com

goddess garden

After discovering our daughter was sensitive to synthetic chemicals, we were inspired to create better alternatives using organic, plant-based ingredients. Our sunscreens go on sheer and provide powerful protection that is safe for people and the planet. Paul and Nova, Founders Reef Safe Non-Nano Biodegradable Non-GMO